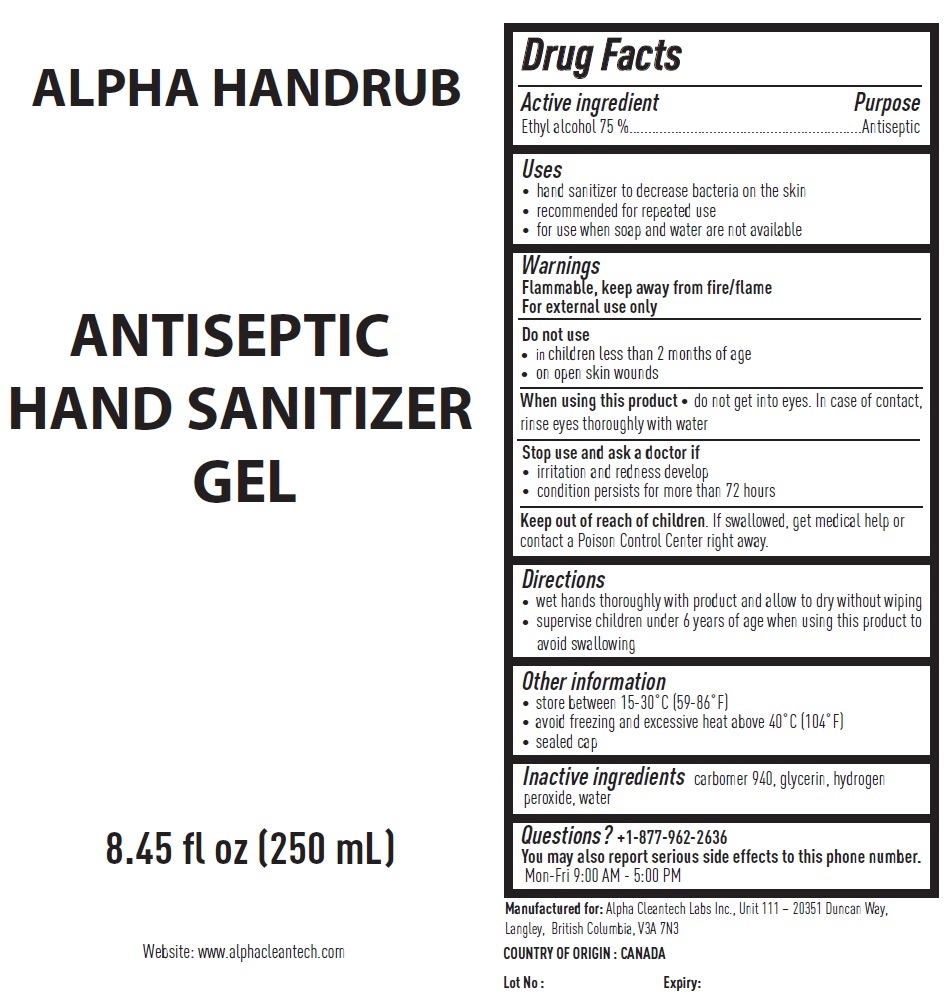 DRUG LABEL: ALPHA HANDRUB ANTISEPTIC HAND SANITIZER
NDC: 77959-202 | Form: GEL
Manufacturer: Alpha Cleantech Labs Inc
Category: otc | Type: HUMAN OTC DRUG LABEL
Date: 20201117

ACTIVE INGREDIENTS: ALCOHOL 75 mL/100 mL
INACTIVE INGREDIENTS: CARBOMER HOMOPOLYMER TYPE C (ALLYL PENTAERYTHRITOL CROSSLINKED); GLYCERIN; HYDROGEN PEROXIDE; WATER

ALPHA HANDRUB ANTISEPTIC HAND SANITIZER GEL

Active ingredient

Ethyl alcohol 75 %

Purpose

Antiseptic

Uses

• hand sanitizer to decrease bacteria on the skin
• recommended for repeated use
• for use when soap and water are not available

Warnings

Flammable, keep away from fire/flame
For external use only

Do not use

• in children less than 2 months of age
• on open skin wounds

When using this product • do not get into eyes. In case of contact, rinse eyes thoroughly with water

Stop use and ask a doctor if
• irritation and redness develop
• condition persists for more than 72 hours

Keep out of reach of children. If swallowed, get medical help or contact a Poison Control Center right away.

Directions

• wet hands thoroughly with product and allow to dry without wiping
• supervise children under 6 years of age when using this product to avoid swallowing

Other information

• store between 15-30°C (59-86°F)
• avoid freezing and excessive heat above 40°C (104°F)
• sealed cap

Inactive ingredients

carbomer 940, glycerin, hydrogen peroxide, water

Questions?

+1-877-962-2636
You may also report serious side effects to this phone number.
Mon-Fri 9:00 AM - 5:00 PM

Manufactured for: Alpha Cleantech Labs Inc., Unit 111 – 20351 Duncan Way,

Langley, British Columbia, V3A 7N3

COUNTRY OF ORIGIN : CANADA

Website: www.alphacleantech.com